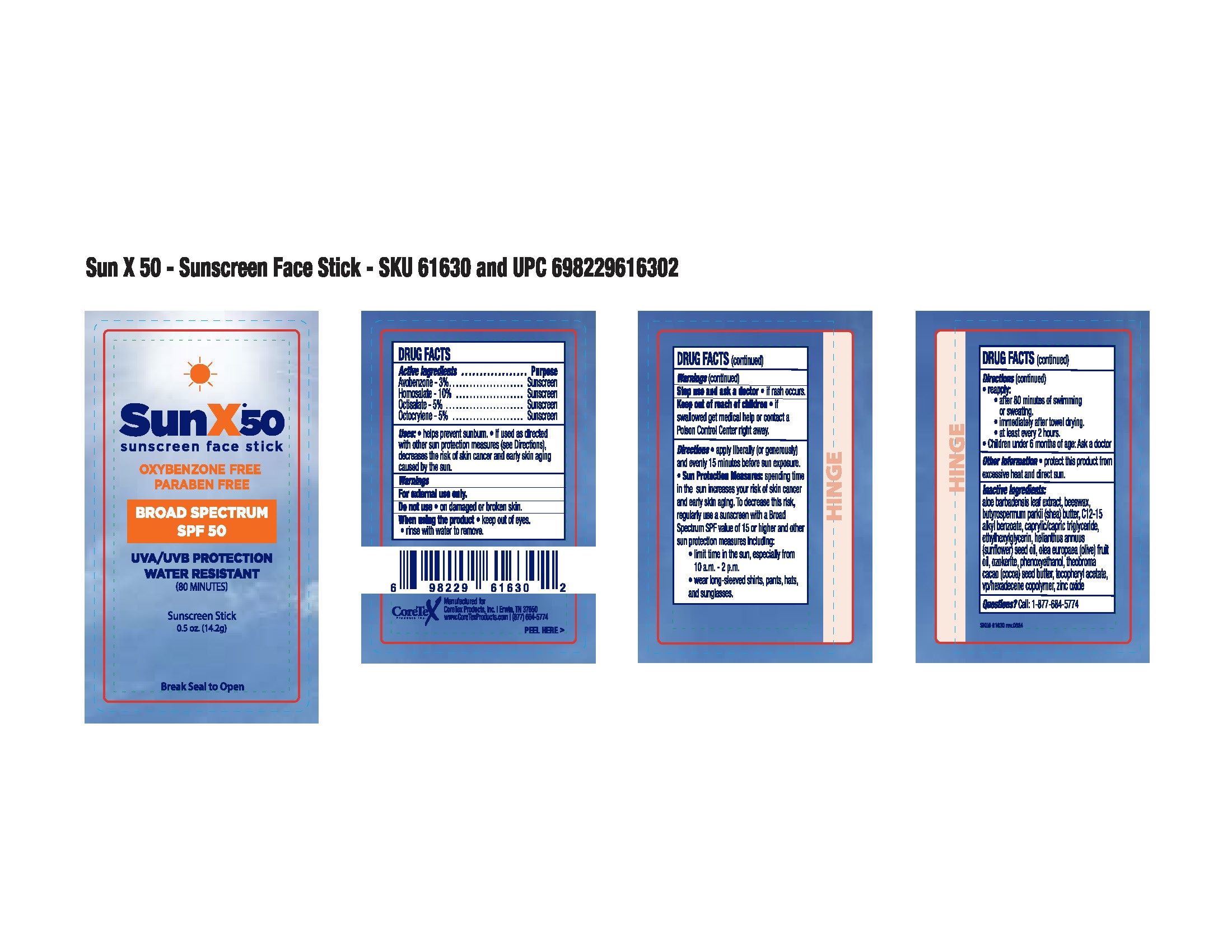 DRUG LABEL: CoreTex SunX 50 Facestick
NDC: 65753-707 | Form: STICK
Manufacturer: CoreTex Products Inc
Category: otc | Type: HUMAN OTC DRUG LABEL
Date: 20250528

ACTIVE INGREDIENTS: AVOBENZONE 3 g/100 g; OCTISALATE 5 g/100 g; OCTOCRYLENE 5 g/100 g; HOMOSALATE 10 g/100 g
INACTIVE INGREDIENTS: C12-15 ALKYL BENZOATE; CAPRYLIC/CAPRIC/LINOLEIC TRIGLYCERIDE; SHEA BUTTER; HELIANTHUS ANNUUS (SUNFLOWER) SEED OIL; PHENOXYETHANOL; THEOBROMA CACAO (COCOA) SEED BUTTER; OLEA EUROPAEA (OLIVE) FRUIT OIL; .ALPHA.-TOCOPHEROL ACETATE; VP/HEXADECENE COPOLYMER; ZINC OXIDE; ALOE BARBADENSIS LEAF; BEESWAX; ETHYLHEXYLGLYCERIN; PARAFFIN

SunX 50 Facestick
65753-707

Active ingredients

Avobenzone 3%

Homosalate 10%

Octisalate 5%

Octocrylene 5%

Purpose

Sunscreen

Sunscreen

Sunscreen

Sunscreen

Uses

- helps prevent sunburn
- if used as directed with other protection measures (see Directions),decreases the risk of skin cancer and early skin aging caused by the sun

Warnings

For external use only

Do not use

- on damaged or broken skin

When using this product

keep out of eyes. Rinse with water to remove

Stop use and ask a doctor if

- rash occurs

Keep out of reach of children

If swallowed get medical help or contact a Poison Control Center right away.

Directions

apply liberally (or generously) and evenly 15 minutes before sun exposure

Sun Protection Measures:spending time in the sun increases your risk of skin cancer and early skin aging. To decrease the risk, regularly use a sunscreen with a Broad Spectrum SPF value of 15 or higher and other sun protection measures including:

- limit time in the sun, especially from 10 a.m. to 2 p.m.
- wear long-sleeved shirt, pants, hat and sunglasses

reapply

- after 80 minutes of swimming or sweating
- immediately after towel drying
- at least every 2 hours

Children under 6 months of age: Ask a doctor.

Other information

- protect the product from excessive heat and direct sun

Inactive ingredients

aloe bardensis leaf extract, beeswax, butyrospermum parkii (shea) butter, C12-15 alkyl benzoate, caprylic/capric triglyceride, ethylhexylglycerin, helianthus annuus (sunflower) seed oil, olea europaea (olive) fruit oil, ozokerite, phenoxyethanol, theobroma cacao (cocoa) seed butter, tocopheryl acetate, vp/hexadecene copolymer, zinc oxide

Questions?

Call 1-877-684-5774